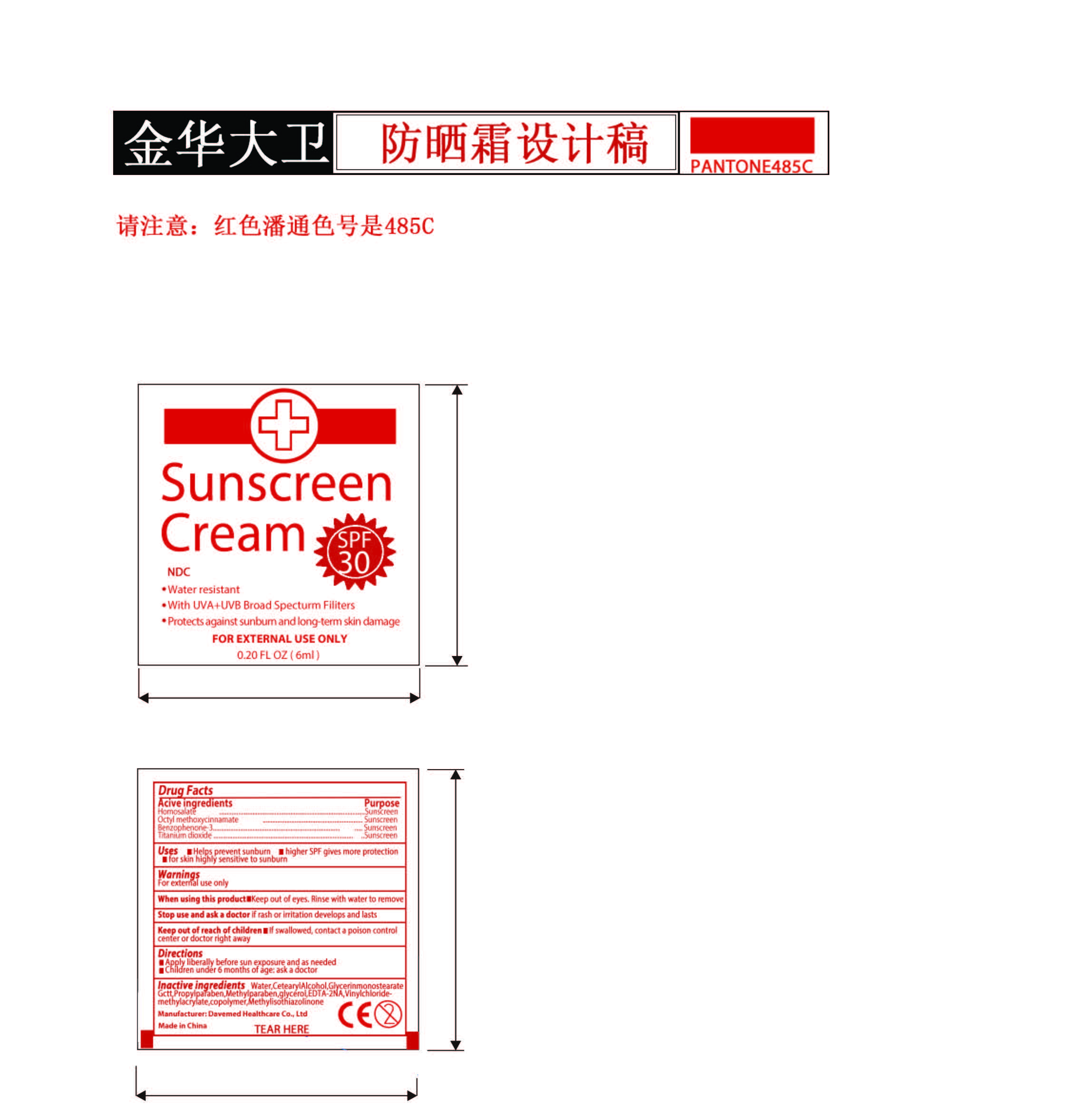 DRUG LABEL: Sunscreen Cream SPF 30
NDC: 70897-008 | Form: CREAM
Manufacturer: Davemed Healthcare Co., Ltd
Category: otc | Type: HUMAN OTC DRUG LABEL
Date: 20190124

ACTIVE INGREDIENTS: HOMOSALATE 4 g/100 mL; TITANIUM DIOXIDE 4 g/100 mL; OXYBENZONE 3 g/100 mL; OCTINOXATE 7 g/100 mL
INACTIVE INGREDIENTS: CETOSTEARYL ALCOHOL; METHYLPARABEN; GLYCERIN; EDETIC ACID; VINYL CHLORIDE; GLATIRAMER ACETATE; DIGLYCERIN MONOSTEARATE; WATER; PROPYLPARABEN; METHYLISOTHIAZOLINONE

Sunscreen Cream SPF 30

Active Ingredients

Active ingredients Purpose

Homosalate..................................Sunscreen

Octyl methoxycinnamate..............Sunscreen

Benzophenone-3..........................Sunscreen

Titanium dioxide...........................Sunscreen

Purpose

Active ingredients Purpose

Homosalate..................................Sunscreen

Octyl methoxycinnamate..............Sunscreen

Benzophenone-3..........................Sunscreen

Titanium dioxide...........................Sunscreen

Uses

- Helps prevent sunburn
- Higher SPF gives more protection
- For skin highly sensitive to sunburn

WARNINGS

For external use only

When using this product

- Keep out eyes. Rinse with water to remove

Stop use and ask a doctor if rash or irritation develops and lasts

KEEP OUT OF REACH OF CHILDREN

- if swallowed, contact a poison control center or doctor right away

Directions

- Apply liberally before sun exposure and as needed
- Children under 6 months of age: ask a doctor

Inactive ingredients

Water, Cetearyl Alcohol, Glycerin monosteareate Gctt, Propylparaben, Methylparaben, glycerol, EDTA-2NA, Vinylchloride-methylacrylate, copolymer, Methylisothiazolinone

Other Information

Store at room temperature